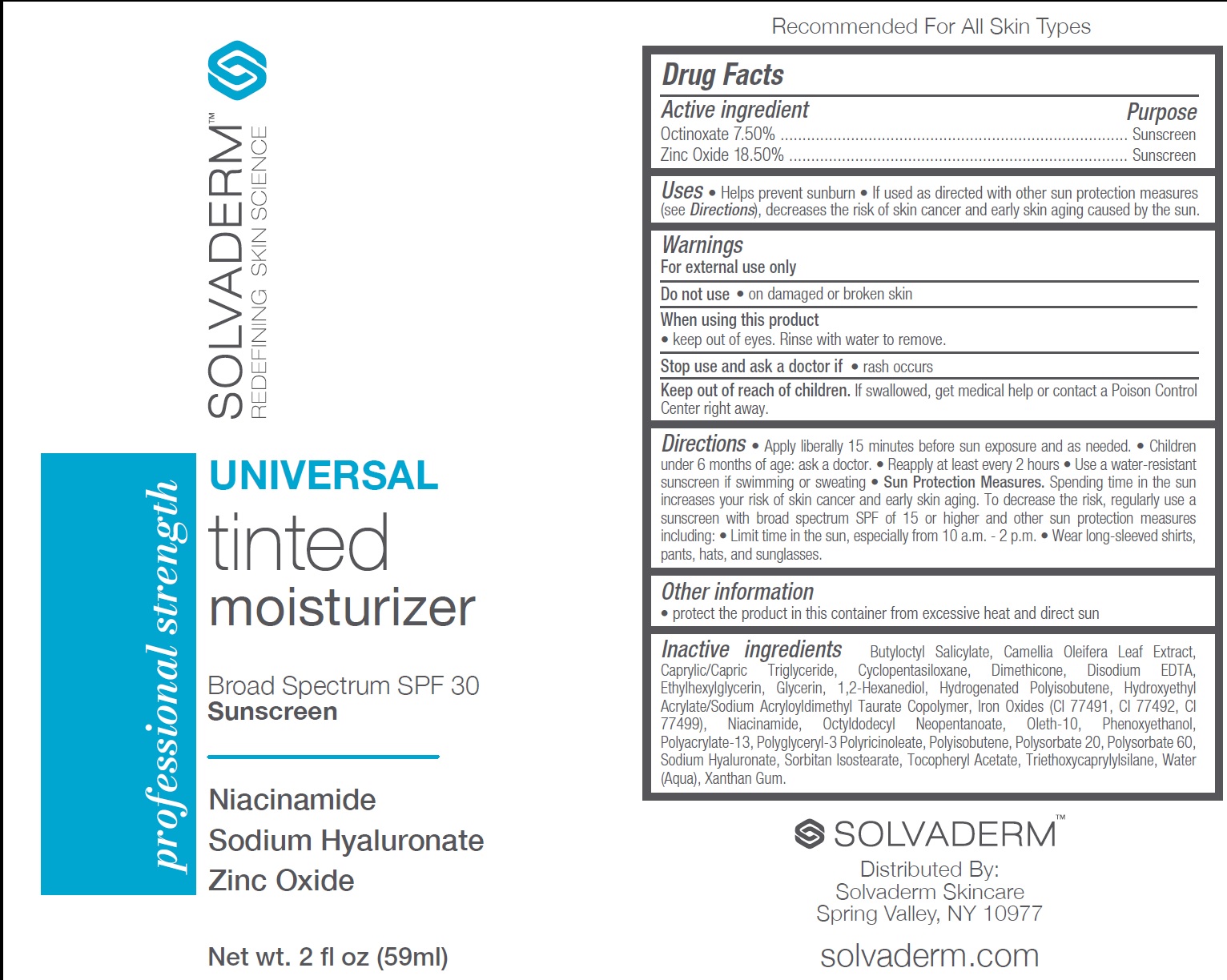 DRUG LABEL: Solvaderm Universal Tinted Moisturizer Sunscreen SPF 30
NDC: 84197-967 | Form: LOTION
Manufacturer: SOLVADERM LLC
Category: otc | Type: HUMAN OTC DRUG LABEL
Date: 20250527

ACTIVE INGREDIENTS: OCTINOXATE 75 mg/1 mL; ZINC OXIDE 185 mg/1 mL
INACTIVE INGREDIENTS: BUTYLOCTYL SALICYLATE; CAMELLIA OLEIFERA LEAF; MEDIUM-CHAIN TRIGLYCERIDES; CYCLOPENTASILOXANE; DIMETHICONE; EDETATE DISODIUM; ETHYLHEXYLGLYCERIN; GLYCERIN; 1,2-HEXANEDIOL; FERRIC OXIDE RED; FERRIC OXIDE YELLOW; FERROSOFERRIC OXIDE; NIACINAMIDE; OCTYLDODECYL NEOPENTANOATE; OLETH-10; PHENOXYETHANOL; POLYACRYLATE-13; POLYSORBATE 20; POLYSORBATE 60; SODIUM HYALURONATE; SORBITAN ISOSTEARATE; .ALPHA.-TOCOPHEROL ACETATE; TRIETHOXYCAPRYLYLSILANE; WATER; XANTHAN GUM

Solvaderm Universal Tinted Moisturizer Sunscreen SPF 30

Active ingredient

Octinoxate 7.50%
Zinc Oxide 18.50%

Purpose

Sunscreen

Uses

- Helps prevent sunburn
- If used as directed with other sun protection measures (see Directions), decreases the risk of skin cancer and early skin aging caused by the sun.

Warnings

For external use only

Do not use

- on damaged or broken skin

When using this product

- keep out of eyes. Rinse with water to remove.

Stop use and ask a doctor if

- rash occurs

Keep out of reach of children.

If swallowed, get medical help or contact a Poison Control Center right away.

Directions

- Apply liberally 15 minutes before sun exposure and as needed.
- Children under 6 months of age: ask a doctor.
- Reapply at least every 2 hours
- Use a water-resistant sunscreen if swimming or sweating
- Sun Protection Measures.Spending time in the sun increases your risk of skin cancer and early skin aging. To decrease the risk, regularly use a sunscreen with broad spectrum SPF of 15 or higher and other sun protection measures including:
- Limit time in the sun, especially from 10 a.m. - 2 p.m.
- Wear long-sleeved shirts, pants, hats, and sunglasses.

Other information

- protect the product in this container from excessive heat and direct sun

Inactive ingredients

Butyloctyl Salicylate, Camellia Oleifera Leaf Extract, Caprylic/Capric Triglyceride, Cyclopentasiloxane, Dimethicone, Disodium EDTA, Ethylhexylglycerin, Glycerin, 1,2-Hexanediol, Hydrogenated Polyisobutene, Hydroxyethyl Acrylate/Sodium Acryloyldimethyl Taurate Copolymer, Iron Oxides (CI 77491, CI 77492, CI 77499), Niacinamide, Octyldodecyl Neopentanoate, Oleth-10, Phenoxyethanol, Polyacrylate-13, Polyglyceryl-3 Polyricinoleate, Polyisobutene, Polysorbate 20, Polysorbate 60, Sodium Hyaluronate, Sorbitan Isostearate, Tocopheryl Acetate, Triethoxycaprylylsilane, Water (Aqua), Xanthan Gum.